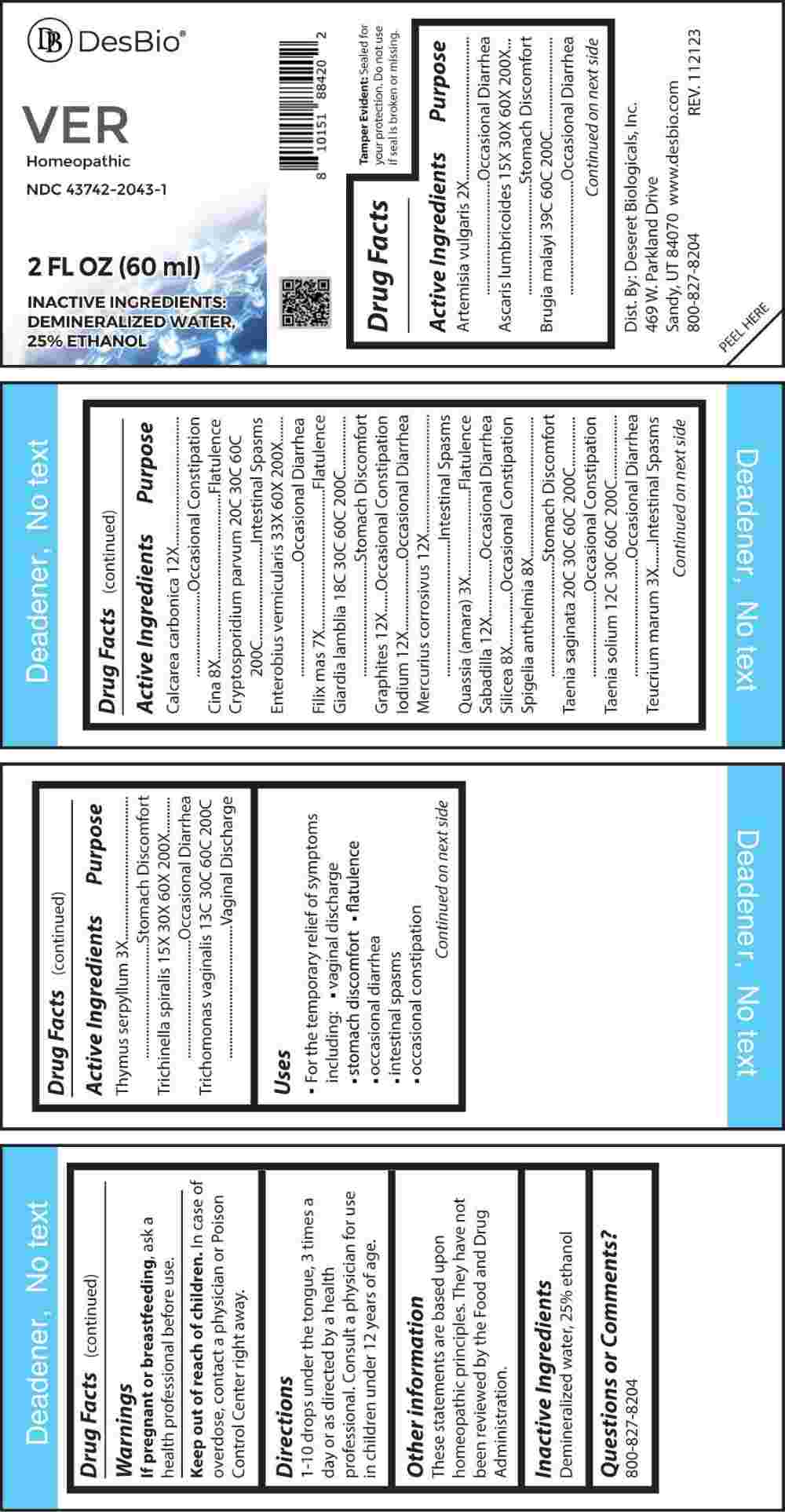 DRUG LABEL: Ver
NDC: 43742-2043 | Form: LIQUID
Manufacturer: Deseret Biologicals, Inc.
Category: homeopathic | Type: HUMAN OTC DRUG LABEL
Date: 20240312

ACTIVE INGREDIENTS: ARTEMISIA VULGARIS ROOT 2 [hp_X]/1 mL; ASCARIS LUMBRICOIDES 15 [hp_X]/1 mL; BRUGIA MALAYI 39 [hp_C]/1 mL; OYSTER SHELL CALCIUM CARBONATE, CRUDE 12 [hp_X]/1 mL; ARTEMISIA CINA PRE-FLOWERING TOP 8 [hp_X]/1 mL; CRYPTOSPORIDIUM PARVUM 20 [hp_C]/1 mL; ENTEROBIUS VERMICULARIS 33 [hp_X]/1 mL; DRYOPTERIS FILIX-MAS ROOT 7 [hp_X]/1 mL; GIARDIA LAMBLIA 18 [hp_C]/1 mL; GRAPHITE 12 [hp_X]/1 mL; IODINE 12 [hp_X]/1 mL; MERCURIC CHLORIDE 12 [hp_X]/1 mL; QUASSIA AMARA WOOD 3 [hp_X]/1 mL; SCHOENOCAULON OFFICINALE SEED 12 [hp_X]/1 mL; SILICON DIOXIDE 8 [hp_X]/1 mL; SPIGELIA ANTHELMIA WHOLE 8 [hp_X]/1 mL; TAENIA SAGINATA 20 [hp_C]/1 mL; TAENIA SOLIUM 12 [hp_C]/1 mL; TEUCRIUM MARUM WHOLE 3 [hp_X]/1 mL; THYMUS SERPYLLUM WHOLE 3 [hp_X]/1 mL; TRICHINELLA SPIRALIS 15 [hp_X]/1 mL; TRICHOMONAS VAGINALIS 13 [hp_C]/1 mL
INACTIVE INGREDIENTS: WATER; ALCOHOL

DRUG FACTS:

ACTIVE INGREDIENTS:

Artemisia Vulgaris 2X, Ascaris Lumbricoides 15X, 30X, 60X, 200X, Brugia Malayi 39C, 60C, 200C, Calcarea Carbonica 12X, Cina 8X, Cryptosporidium Parvum 20C, 30C, 60C, 200C, Enterobius Vermicularis 33X, 60X, 200X, Filix Mas 7X, Giardia Lamblia 18C, 30C, 60C, 200C, Graphites 12X, Iodium 12X, Mercurius Corrosivus 12X, Quassia (Amara) 3X, Sabadilla 12X, Silicea 8X, Spigelia Anthelmia 8X, Taenia Saginata 20C, 30C, 60C, 200C, Taenia Solium 12C, 30C, 60C, 200C, Teucrium Marum 3X, Thymus Serpyllum 3X, Trichinella Spiralis 15X, 30X, 60X, 200X, Trichomonas Vaginalis 13C, 30C, 60C, 200C.

PURPOSE:

Artemisia Vulgaris – Occasional Diarrhea, Ascaris Lumbricoides – Stomach Discomfort, Brugia Malayi – Occasional Diarrhea, Calcarea Carbonica – Occasional Constipation, Cina - Flatulence, Cryptosporidium Parvum – Intestinal Spasms, Enterobius Vermicularis – Occasional Diarrhea, Filix Mas - Flatulence, Giardia Lamblia – Stomach Discomfort, Graphites – Occasional Constipation, Iodium – Occasional Diarrhea, Mercurius Corrosivus – Intestinal Spasms, Quassia (Amara) - Flatulence, Sabadilla – Occasional Diarrhea, Silicea – Occasional Constipation, Spigelia Anthelmia – Stomach Discomfort, Taenia Saginata – Occasional Constipation, Taenia Solium – Occasional Diarrhea, Teucrium Marum – Intestinal Spasms, Thymus Serpyllum – Stomach Discomfort, Trichinella Spiralis – Occasional Diarrhea, Trichomonas Vaginalis – Vaginal Discharge.

USES:

• For the temporary relief of symptoms including:

• vaginal discharge • stomach discomfort • flatulence

• occasional diarrhea • intestinal spasms

• occasional constipation

These statements are based upon homeopathic principles. They have not been reviewed by the Food and Drug Administration.

WARNINGS:

If pregnant or breast-feeding, ask a health professional before use.

Keep out of reach of children. In case of overdose, contact a physician or Poison Control Center right away.

Tamper Evident: Sealed for your protection. Do not use if seal is broken or missing.

KEEP OUT OF REACH OF CHILDREN:

In case of overdose, contact a physician or Poison Control Center right away.

DIRECTIONS:

1-10 drops under the tongue, 3 times a day or as directed by a health professional. Consult a physician for use in children under 12 years of age.

INACTIVE INGREDIENTS:

Demineralized water, 25% ethanol

QUESTIONS:

Dist. By: Deseret Biologicals, Inc.

469 W. Parkland Drive

Sandy, UT 84070

www.desbio.com

800-827-8204

PACKAGE LABEL DISPLAY:

Des Bio

VER

Homeopathic

NDC 43742-2043-1

2 FL OZ (60 ml)